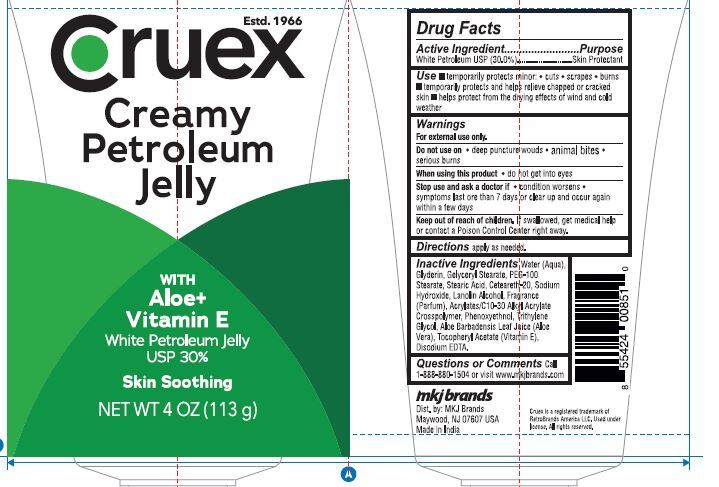 DRUG LABEL: Cruex Petroleum Jelly
NDC: 77782-004 | Form: JELLY
Manufacturer: MKJ BRANDS LLC
Category: otc | Type: HUMAN OTC DRUG LABEL
Date: 20251210

ACTIVE INGREDIENTS: PETROLATUM 30 g/100 g
INACTIVE INGREDIENTS: LANOLIN ALCOHOL; PHENOXYETHANOL; ACRYLATES/C10-30 ALKYL ACRYLATE CROSSPOLYMER (60000 MPA.S); STEARIC ACID; AQUA; GLYCERIN; CETEARETH-20; .ALPHA.-TOCOPHEROL ACETATE; ALOE BARBADENSIS LEAF; EDETATE DISODIUM; PEG-100 MONOSTEARATE; TRIETHYLENE GLYCOL; GLYCERYL STEARATE; SODIUM HYDROXIDE

Cruex Petroleum Jelly

Drug Facts

Active Ingredient

White Petrolatum USP 30%

Purpose

Skin protectant

Uses

temporarily protects ■ minor cuts, scrapes,
burns ■ and help relieve chapped or cracked
skin and lips ■ from the drying effects of wind and
cold weather

Warnings

For external use only

When using this product

do not get into eyes

Stop use and consult a doctor

if the condition lasts more than 7 days.

Do not use on

■ deep or puncture wounds
■ animal bites ■ serious burns

Keep out of reach of children

If swallowed, get medical help or contact a Poison Control Center right away. (1-800-222-1222)

Directions

apply as needed

INACTIVE INGREDIENT

Aloe barbadensis leaf extract, frafrance, tocopheryl acetate, water, glycerin, gelyceryl stearate, PEG-100 Stearate, stearic acid, sodium hydroxide, Lanolin alcohol, Fragrance, Acrylates 10-30 alkyl acrylate crosspolymer, pheonxyethanol, triethylene glycol, dospdoium EDTA